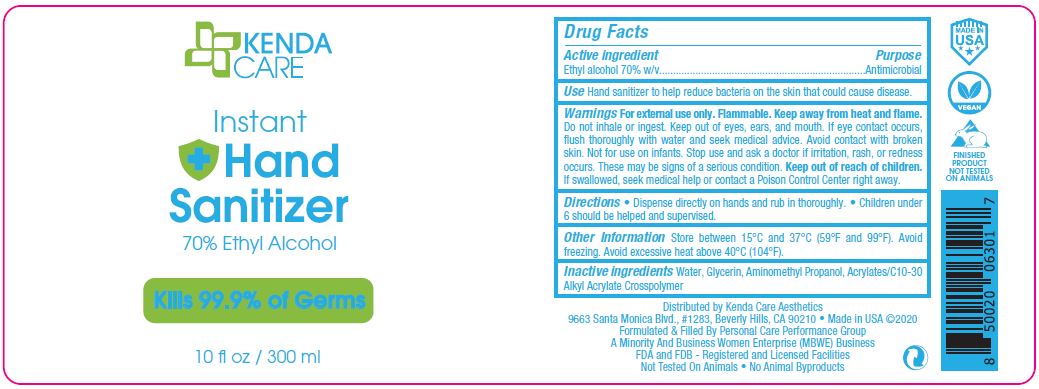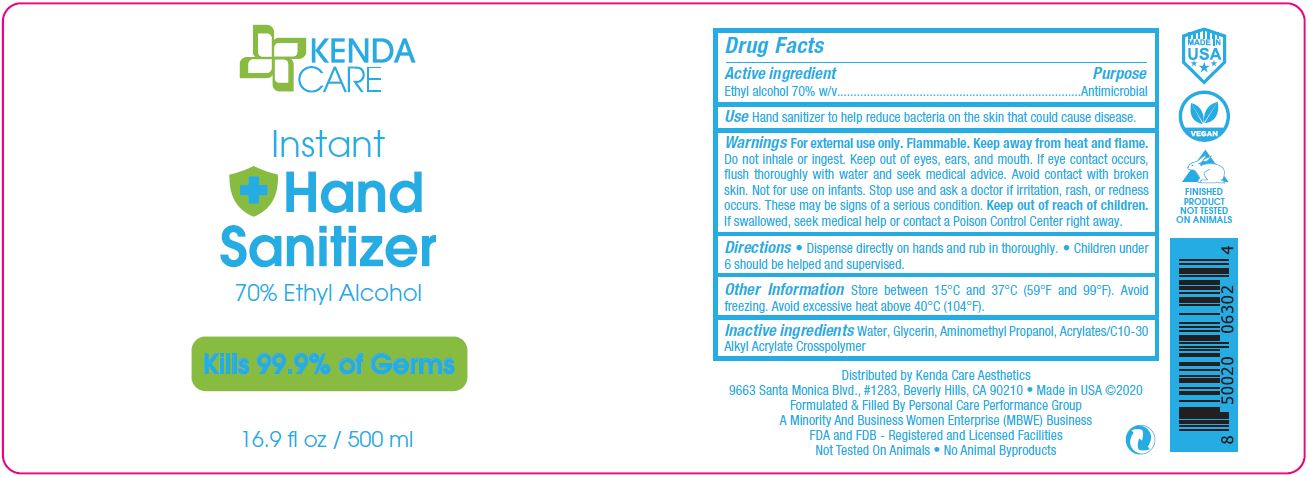 DRUG LABEL: KENDA CARE INSTANT HAND SANITIZER

NDC: 76038-404 | Form: GEL
Manufacturer: MICRO CONNECTION ENTERPRISES INC
Category: otc | Type: HUMAN OTC DRUG LABEL
Date: 20230301

ACTIVE INGREDIENTS: ALCOHOL 70 mL/100 mL
INACTIVE INGREDIENTS: CARBOMER INTERPOLYMER TYPE A (ALLYL SUCROSE CROSSLINKED); AMINOMETHYLPROPANOL; GLYCERIN; WATER

PCPG (as CMO) - KENDA CARE INSTANT HAND SANITIZER - 70% ETHYL ALCOHOL (76038-404)

ACTIVE INGREDIENT

ETHYL ALCOHOL 70% W/V

PURPOSE

ANTIMICROBIAL

USE

Hand sanitizer to help reduce bacteria on the skin that could cause disease.

WARNINGS

For external use only. Flammable. Keep away from heat and flame. Do not inhale or ingest. Keep out of eyes, ears, and mouth. If eye contact occurs, flush thoroughly with water and seek medical advice. Avoid contact with broken skin. Not for use on infants. Stop use and ask a doctor if irritation, rash, or redness occurs. These may be signs of a serious condition.

Keep out of reach of children. If swallowed, seek medical help or contact a Poison Control Center right away.

DIRECTIONS

- Dispense directly on hands and rub in thoroughly.
- Children under 6 should be helped and supervised.

OTHER INFORMATION

Store between 15°C and 37°C (59°F and 99°F). Avoid freezing. Avoid excessive heat above 40°C (104°F).

INACTIVE INGREDIENTS

Water, Glycerin, Aminomethyl Propanol, Acrylates/C10-30 Alkyl Acrylate Crosspolymer